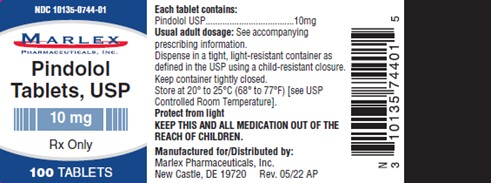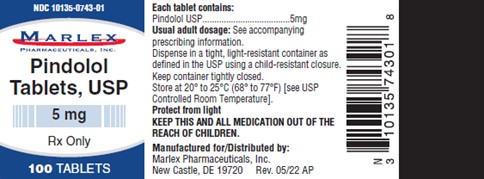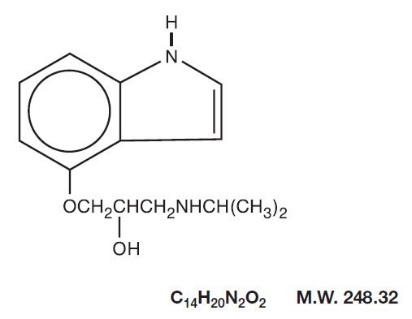 DRUG LABEL: Pindolol
NDC: 10135-743 | Form: TABLET
Manufacturer: Marlex Pharmaceuticals, Inc.
Category: prescription | Type: HUMAN PRESCRIPTION DRUG LABEL
Date: 20260206

ACTIVE INGREDIENTS: PINDOLOL 5 mg/1 1
INACTIVE INGREDIENTS: MICROCRYSTALLINE CELLULOSE; SILICON DIOXIDE; MAGNESIUM STEARATE; STARCH, CORN

PINDOLOL TABLETS USP

DESCRIPTION

Pindolol, a synthetic beta-adrenergic receptor blocking agent with intrinsic sympathomimetic activity is 1-(Indol-4-yloxy)-3-(isopropylamino)-2-propanol.

Pindolol, USP is a white to off-white, crystalline powder having a faint odor which is practically insoluble in water; slightly soluble in methanol; and very slightly soluble in chloroform.

Each tablet for oral administration contains pindolol and the following inactive ingredients: microcrystalline cellulose, pregelatinized starch, colloidal silicon dioxide and magnesium stearate.

CLINICAL PHARMACOLOGY

Pindolol is a nonselective beta-adrenergic antagonist (beta-blocker) which possesses intrinsic sympathomimetic activity (ISA) in therapeutic dosage ranges but does not possess quinidine-like membrane stabilizing activity.

PHARMACODYNAMICS

In standard pharmacologic tests in man and animals, pindolol attenuates increases in heart rate, systolic blood pressure, and cardiac output resulting from exercise and isoproterenol administration, thus confirming its beta-blocking properties. The ISA or partial agonist activity of pindolol is mediated directly at the adrenergic receptor sites and may be blocked by other beta-blockers. In catecholamine depleted animal experiments, ISA is manifested as an increase in the inotropic and chronotropic activity of the myocardium. In man, ISA is manifested by a smaller reduction in the resting heart rate (4 to 8 beats/min) than is seen with drugs lacking ISA. There is also a smaller reduction in resting cardiac output. The clinical significance of this observation has not been evaluated and there is no evidence, or reason to believe, that exercise cardiac output is less affected by pindolol.

Pindolol has been shown in controlled, double-blind clinical studies to be an effective antihypertensive agent when used as monotherapy, or when added to therapy with thiazide-type diuretics. Divided dosages in the range of 10 mg to 60 mg daily have been shown to be effective. As monotherapy, pindolol is as effective as propranolol, α-methyldopa, hydrochlorothiazide, and chlorthalidone in reducing systolic and diastolic blood pressure. The effect on blood pressure is not orthostatic, i.e., pindolol was equally effective in reducing the supine and standing blood pressure.

In open, long-term studies up to 4 years, no evidence of diminution of the blood pressure lowering response was observed.

An average 3-pound increase in body weight has been noted in patients treated with pindolol alone, a larger increase than was observed with propranolol or placebo. The weight gain appeared unrelated to blood pressure response and was not associated with an increased risk of heart failure, although edema was more common than in control patients. Pindolol does not have a consistent effect on plasma renin activity.

The mechanism of the antihypertensive effects of beta-blocking agents has not been established, but several mechanisms have been postulated: 1) an effect on the central nervous system resulting in a reduced sympathetic outflow to the periphery, 2) competitive antagonism of catecholamines at peripheral (especially cardiac) adrenergic receptor sites, leading to decreased cardiac output, 3) an inhibition of renin release. These mechanisms appear less likely for pindolol than other beta-blockers in view of the modest effect on resting cardiac output and renin.

Beta-blockade therapy is useful when it is necessary to suppress the effects of beta-adrenergic agonists in order to achieve therapeutic goals. However, in certain clinical situations, (e.g., cardiac failure, heart block, bronchospasm), the preservation of an adequate sympathetic tone may be necessary to maintain vital functions. Although a beta-antagonist with ISA such as pindolol does not eliminate sympathetic tone entirely, there is no controlled evidence that it is safer than other beta-blockers in such conditions as heart failure, heart block, or bronchospasm or is less likely to cause those conditions. In single-dose studies of the effects of beta-blockers on FEV1, pindolol was indistinguishable from other non-cardioselective agents in its reduction of FEV1, and its reduction in the effectiveness of an exogenous beta-agonist.

Exacerbation of angina and, in some cases, myocardial infarction and ventricular dysrhythmias have been reported after abrupt discontinuation of therapy with beta-adrenergic blocking agents in patients with coronary artery disease. Abrupt withdrawal of these agents in patients without coronary artery disease has resulted in transient symptoms, including tremulousness, sweating, palpitation, headache, and malaise. Several mechanisms have been proposed to explain these phenomena, among them increased sensitivity to catecholamines because of increased numbers of beta receptors.

PHARMACOKINETICS AND METABOLISM

Pindolol is rapidly and reproducibly absorbed (greater than 95%), achieving peak plasma concentrations within 1 hour of drug administration. Pindolol has no significant first-pass effect. The blood concentrations are proportional in a linear manner to the administered dose in the range of 5 mg to 20 mg. Upon repeated administration to the same subject, variation is minimal. After a single dose, intersubject variation for peak plasma concentrations was about 4-fold (e.g., 45 to 167 ng/mL for a 20 mg dose). Upon multiple dosing, intersubject variation decreased to 2- to 2.5-fold. Pindolol is only 40% bound to plasma proteins and is evenly distributed between plasma and red cells. The volume of distribution in healthy subjects is about 2 L/kg.

Pindolol undergoes extensive metabolism in animals and man. In man, 35% to 40% is excreted unchanged in the urine and 60% to 65% is metabolized primarily to hydroxy-metabolites which are excreted as glucuronides and ethereal sulfates. The polar metabolites are excreted with a half-life of approximately 8 hours and thus multiple dosing therapy (q.8H) results in a less than 50% accumulation in plasma. About 6% to 9% of an administered intravenous dose is excreted by the bile into the feces.

The disposition of pindolol after oral administration is monophasic with a half-life in healthy subjects or hypertensive patients with normal renal function of approximately 3 to 4 hours. Following t.i.d. administration (q.8H), no significant accumulation of pindolol is observed.

In elderly hypertensive patients with normal renal function, the half-life of pindolol is more variable, averaging about 7 hours, but with values as high as 15 hours.

In hypertensive patients with renal diseases, the half-life is within the range expected for healthy subjects. However, a significant decrease (50%) in volume of distribution (VD) is observed in uremic patients and VDappears to be directly correlated to creatinine clearance. Therefore, renal drug clearance is significantly reduced in uremic patients, resulting in a significant decrease in urinary excretion of unchanged drug. Uremic patients with a creatinine clearance of less than 20 mL/min generally excreted less than 15% of the administered dose unchanged in the urine.

In patients with histologically diagnosed cirrhosis of the liver, the elimination of pindolol was more variable in rate and generally significantly slower than in healthy subjects. The total body clearance of pindolol in cirrhotic patients ranged from about 50 to 300 mL/min and was directly correlated to antipyrine clearance. The half-life ranges from 2.5 hours to greater than 30 hours. These findings strongly suggest that caution should be exercised in dosage adjustments of pindolol in such patients.

The bioavailability of pindolol is not significantly affected by coadministration of food, hydralazine, hydrochlorothiazide or aspirin. Pindolol has no effect on warfarin activity or the clinical effectiveness of digoxin, although small transient decreases in plasma digoxin concentrations were noted.

INDICATIONS AND USAGE

Pindolol tablets are indicated in the management of hypertension. It may be used alone or concomitantly with other antihypertensive agents, particularly with a thiazide-type diuretic.

CONTRAINDICATIONS

Pindolol tablets are contraindicated in: 1) bronchial asthma; 2) overt cardiac failure; 3) cardiogenic shock; 4) second and third degree heart block; 5) severe bradycardia. (See WARNINGS.)

WARNINGS

Cardiac Failure

Sympathetic stimulation may be a vital component supporting circulatory function in patients with congestive heart failure, and its inhibition by beta-blockade may precipitate more severe failure. Although beta-blockers should be avoided in overt congestive heart failure, if necessary, pindolol can be used with caution in patients with a history of failure who are well-compensated, usually with digitalis and diuretics. Both digitalis glycosides and beta-blockers slow atrioventricular conduction and decrease heart rate. Concomitant use can increase risk of bradycardia. Beta-adrenergic blocking agents do not abolish the inotropic action of digitalis on heart muscle.

In Patients Without A History of Cardiac Failure

In patients with latent cardiac insufficiency, continued depression of the myocardium with beta-blocking agents over a period of time can in some cases lead to cardiac failure. At the first sign or symptom of impending cardiac failure, patients should be fully digitalized and/or be given a diuretic, and the response observed closely. If cardiac failure continues, despite adequate digitalization and diuretic, pindolol therapy should be withdrawn (gradually, if possible).

Exacerbation of Ischemic Heart Disease Following Abrupt Withdrawal

Hypersensitivity to catecholamines has been observed in patients withdrawn from beta-blocker therapy; exacerbation of angina and, in some cases, myocardial infarction have occurred after abruptdiscontinuation of such therapy. When discontinuing chronically administered pindolol, particularly in patients with ischemic heart disease, the dosage should be gradually reduced over a period of 1 to 2 weeks and the patient should be carefully monitored. If angina markedly worsens or acute coronary insufficiency develops, pindolol administration should be reinstituted promptly, at least temporarily, and other measures appropriate for the management of unstable angina should be taken. Patients should be warned against interruption or discontinuation of therapy without the physician’s advice. Because coronary artery disease is common and may be unrecognized, it may be prudent not to discontinue pindolol therapy abruptly even in patients treated only for hypertension.

Nonallergic Bronchospasm (e.g., chronic bronchitis, emphysema) - Patients with Bronchospastic Diseases Should in General Not Receive Beta-Blockers

Pindolol should be administered with caution since it may block bronchodilation produced by endogenous or exogenous catecholamine stimulation of beta2receptors.

Major Surgery

Because beta-blockade impairs the ability of the heart to respond to reflex stimuli and may increase the risks of general anesthesia and surgical procedures, resulting in protracted hypotension or low cardiac output, it has generally been suggested that such therapy should be gradually withdrawn several days prior to surgery. Recognition of the increased sensitivity to catecholamines of patients recently withdrawn from beta-blocker therapy, however, has made this recommendation controversial. If possible, beta-blockers should be withdrawn well before surgery takes place. In the event of emergency surgery, the anesthesiologist should be informed that the patient is on beta-blocker therapy.

The effects of pindolol can be reversed by administration of beta-receptor agonists such as isoproterenol, dopamine, dobutamine, or norepinephrine. Difficulty in restarting and maintaining the heart beat has also been reported with beta-adrenergic receptor blocking agents.

Diabetes and Hypoglycemia

Beta-adrenergic blockade may prevent the appearance of premonitory signs and symptoms (e.g., tachycardia and blood pressure changes) of acute hypoglycemia. This is especially important with labile diabetics. Beta-blockade also reduces the release of insulin in response to hyperglycemia; therefore, it may be necessary to adjust the dose of antidiabetic drugs.

Thyrotoxicosis

Beta-adrenergic blockade may mask certain clinical signs (e.g., tachycardia) of hyperthyroidism. Patients suspected of developing thyrotoxicosis should be managed carefully to avoid abrupt withdrawal of beta-blockade which might precipitate a thyroid crisis.

PRECAUTIONS

Impaired Renal or Hepatic Function

Beta-blocking agents should be used with caution in patients with impaired hepatic or renal function. Poor renal function has only minor effects on pindolol clearance, but poor hepatic function may cause blood levels of pindolol to increase substantially.

Information for Patients

Patients, especially those with evidence of coronary artery insufficiency, should be warned against interruption or discontinuation of pindolol therapy without the physician’s advice. Although cardiac failure rarely occurs in properly selected patients, patients being treated with beta-adrenergic blocking agents should be advised to consult the physician at the first sign or symptom of impending failure.

Drug Interactions

Catecholamine-depleting drugs (e.g., reserpine) may have an additive effect when given with beta-blocking agents. Patients receiving pindolol plus a catecholamine-depleting agent should, therefore, be closely observed for evidence of hypotension and/or marked bradycardia which may produce vertigo, syncope, or postural hypotension.

Pindolol has been used with a variety of antihypertensive agents, including hydrochlorothiazide, hydralazine, and guanethidine without unexpected adverse interactions.

Pindolol has been shown to increase serum thioridazine levels when both drugs are coadministered. Pindolol levels may also be increased with this combination.

Risk of Anaphylactic Reaction

While taking beta blockers, patients with a history of severe anaphylactic reaction to a variety of allergens may be more reactive to repeated challenge, either accidental, diagnostic, or therapeutic. Such patients may be unresponsive to the usual doses of epinephrine used to treat allergic reactions.

Carcinogenesis, Mutagenesis, Impairment of Fertility

In chronic oral toxicologic studies (1 to 2 years) in mice, rats, and dogs, pindolol did not produce any significant toxic effects. In 2-year oral carcinogenicity studies in rats and mice in doses as high as 59 mg/kg/day and 124 mg/kg/day (50 and 100 times the maximum recommended human dose), respectively, pindolol did not produce any neoplastic, preneoplastic, or nonneoplastic pathologic lesions. In fertility and general reproductive performance studies in rats, pindolol caused no adverse effects at a dose of 10 mg/kg.

In the male fertility and general reproductive performance test in rats, definite toxicity characterized by mortality and decreased weight gain was observed in the group given 100 mg/kg/day. At 30 mg/kg/day, decreased mating was associated with testicular atrophy and/or decreased spermatogenesis. This response is not clearly drug-related, however, as there was no dose-response relationship within this experiment and no similar effect on testes of rats administered pindolol as a dietary admixture for 104 weeks. There appeared to be an increase in prenatal mortality in males given 100 mg/kg but development of offspring was not impaired.

In females administered pindolol prior to mating through day 21 of lactation, mating behavior was decreased at 100 mg/kg and 30 mg/kg. At these dosages there also was increased mortality of offspring. Prenatal mortality was increased at 10 mg/kg but there was not a clear dose-response relationship in this experiment. There was an increased resorption rate at 100 mg/kg observed in females necropsied on the 15th day of gestation.

Pregnancy

Teratogenic Effects. Category B

Studies in rats and rabbits exceeding 100 times the maximum recommended human doses, revealed no embryotoxicity or teratogenicity. Since there are no adequate and well controlled studies in pregnant women, and since animal reproduction studies are not always predictive of human response, pindolol, as with any drug, should be employed during pregnancy only if the potential benefit justifies the potential risk to the fetus.

Nursing Mothers

Since pindolol is secreted in human milk, nursing should not be undertaken by mothers receiving the drug.

Pediatric Use

Safety and effectiveness in pediatric patients have not been established.

CLINICAL LABORATORY

Minor persistent elevations in serum transaminases (SGOT, SGPT) have been noted in 7% of patients during pindolol administration, but progressive elevations were not observed. These elevations were not associated with any other abnormalities that would suggest hepatic impairment, such as decreased serum albumin and total proteins. During more than a decade of worldwide marketing, there have been no reports in the medical literature of overt hepatic injury. Alkaline phosphatase, lactic acid dehydrogenase (LDH), and uric acid are also elevated on rare occasions. The significance of these findings is unknown.

ADVERSE REACTIONS

Most adverse reactions have been mild. The incidences listed in the following table are derived from 12-week comparative double-blind, parallel design trials in hypertensive patients given pindolol as monotherapy, given various active control drugs as monotherapy, or given placebo. Data for pindolol and the positive controls were pooled from several trials because no striking differences were seen in the individual studies, with one exception. When considering all adverse reactions reported, the frequency of edema was noticeably higher in positive control trials (16% pindolol vs. 9% positive control) than in placebo controlled trials (6% pindolol vs. 3% placebo). The table includes adverse reactions either volunteered or elicited, and at least possibly drug-related, which were reported in greater than 2% of pindolol patients and other selected important reactions.

ADVERSE REACTIONS WHICH WERE VOLUNTEERED OR ELICITED
(and at least possibly drug-related)
 | Pindolol (N = 322) % | Active Controls* (N = 188) % | Placebo (N = 78) %
Body System/ Adverse Reactions
Central Nervous System
1. Bizarre or Many Dreams | 5 | 0 | 6
1. Dizziness | 9 | 11 | 1
1. Fatigue | 8 | 4 | 4
1. Hallucinations | <1 | 0 | 0
1. Insomnia | 10 | 3 | 10
1. Nervousness | 7 | 3 | 5
1. Weakness | 4 | 2 | 1
Autonomic Nervous System
1. Paresthesia | 3 | 1 | 6
Cardiovascular
1. Dyspnea | 5 | 4 | 6
1. Edema | 6 | 3 | 1
1. Heart Failure | <1 | <1 | 0
1. Palpitations | <1 | 1 | 0
Musculoskeletal
1. Chest Pain | 3 | 1 | 3
1. Joint Pain | 7 | 4 | 4
1. Muscle Cramps | 3 | 1 | 0
1. Muscle Pain | 10 | 9 | 8
Gastrointestinal
1. Abdominal Discomfort | 4 | 4 | 5
1. Nausea | 5 | 2 | 1
Skin
1. Pruritus | 1 | <1 | 0
1. Rash | <1 | <1 | 1

* Active Controls: Patients received either propranolol, α-methyldopa or a diuretic (hydrochlorothiazide or chlorthalidone).

The following selected (potentially important) adverse reactions were seen in 2% or fewer patients and their relationship to pindolol is uncertain. CENTRAL NERVOUS SYSTEM: anxiety, lethargy; AUTONOMIC NERVOUS SYSTEM: visual disturbances, hyperhidrosis; CARDIOVASCULAR: bradycardia, claudication, cold extremities, heart block, hypotension, syncope, tachycardia, weight gain; GASTROINTESTINAL: diarrhea, vomiting; RESPIRATORY: wheezing; UROGENITAL: impotence, pollakiuria; MISCELLANEOUS: eye discomfort or burning eyes.

POTENTIAL ADVERSE EFFECTS

In addition, other adverse effects not aforementioned have been reported with other beta-adrenergic blocking agents and should be considered potential adverse effects of pindolol.

Central Nervous System: Reversible mental depression progressing to catatonia; an acute reversible syndrome characterized by disorientation for time and place, short-term memory loss, emotional lability, slightly clouded sensorium, and decreased performance on neuropsychometrics.

Cardiovascular:Intensification of AV block. (See CONTRAINDICATIONS.)

Allergic:Erythematous rash; fever combined with aching and sore throat; laryngospasm; respiratory distress.

Hematologic:Agranulocytosis; thrombocytopenic and nonthrombocytopenic purpura.

Gastrointestinal:Mesenteric arterial thrombosis; ischemic colitis.

Miscellaneous:Reversible alopecia; Peyronie’s disease.

The oculomucocutaneous syndrome associated with the beta-blocker practolol has not been reported with pindolol during investigational use and extensive foreign experience amounting to over 4 million patient-years.

OVERDOSAGE

No specific information on emergency treatment of overdosage is available. Therefore, on the basis of the pharmacologic actions of pindolol, the following general measures should be employed as appropriate in addition to gastric lavage:

Excessive Bradycardia:administer atropine; if there is no response to vagal blockade, administer isoproterenol cautiously.

Cardiac Failure:digitalize the patient and/or administer diuretic. It has been reported that glucagon may be useful in this situation.

Hypotension:administer vasopressors, e.g., epinephrine or norepinephrine, with serial monitoring of blood pressure. (There is evidence that epinephrine may be the drug of choice.)

Bronchospasm:administer a beta2stimulating agent such as isoproterenol and/or a theophylline derivative.

A case of an acute overdosage has been reported with an intake of 500 mg of pindolol by a hypertensive patient. Blood pressure increased and heart rate was ≥ 80 beats/min. Recovery was uneventful. In another case, 250 mg of pindolol was taken with 150 mg diazepam and 50 mg nitrazepam, producing coma and hypotension. The patient recovered in 24 hours.

DOSAGE AND ADMINISTRATION

The dosage of pindolol tablets should be individualized. The recommended initial dose of pindolol tablets is 5 mg b.i.d. alone or in combination with other antihypertensive agents. An antihypertensive response usually occurs within the first week of treatment. Maximal response, however, may take as long as or occasionally longer than 2 weeks. If a satisfactory reduction in blood pressure does not occur within 3 to 4 weeks, the dose may be adjusted in increments of 10 mg/day at these intervals up to a maximum of 60 mg/day.

HOW SUPPLIED

Pindolol Tablets USP are available as 5 mg and 10 mg tablets.

The 5 mg tablets are a 1/4”, round, white, standard cup tablet, scored, debossed GG 438on one side and plain on the reverse side. They are available in bottles of 100 tablets (NDC 10135-0743-01).

The 10 mg tablets are a 5/16”, round, white, standard cup tablet, scored, debossed GG 439on one side and plain on the reverse side. They are available in bottles of 100 tablets (NDC 10135-0744-01).

Store at 20° to 25°C (68° to 77°F). [See USP Controlled Room Temperature].

Protect from light.

Dispense in a tight, light-resistant container as defined in the USP using a child-resistant closure.

All trademarks are the property of their respective owners.

Manufactured for/ Distributed by:

Marlex Pharmaceuticals, Inc.

New Castle, DE 19720

Rev. 05/22 AP

PACKAGE/LABEL PRINCIPAL DISPLAY PANEL

Pindolol Tablets USP, 5 mg
NDC 10135-0743-01
Rx only
100 Tablets

PACKAGE/LABEL PRINCIPAL DISPLAY PANEL

Pindolol Tablets USP, 10 mg
NDC 10135-0744-01
Rx only
100 Tablets